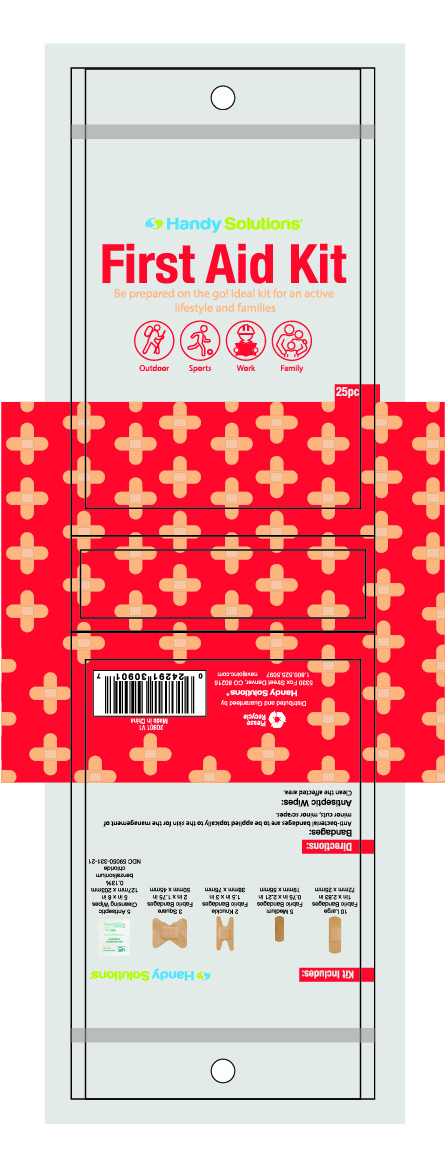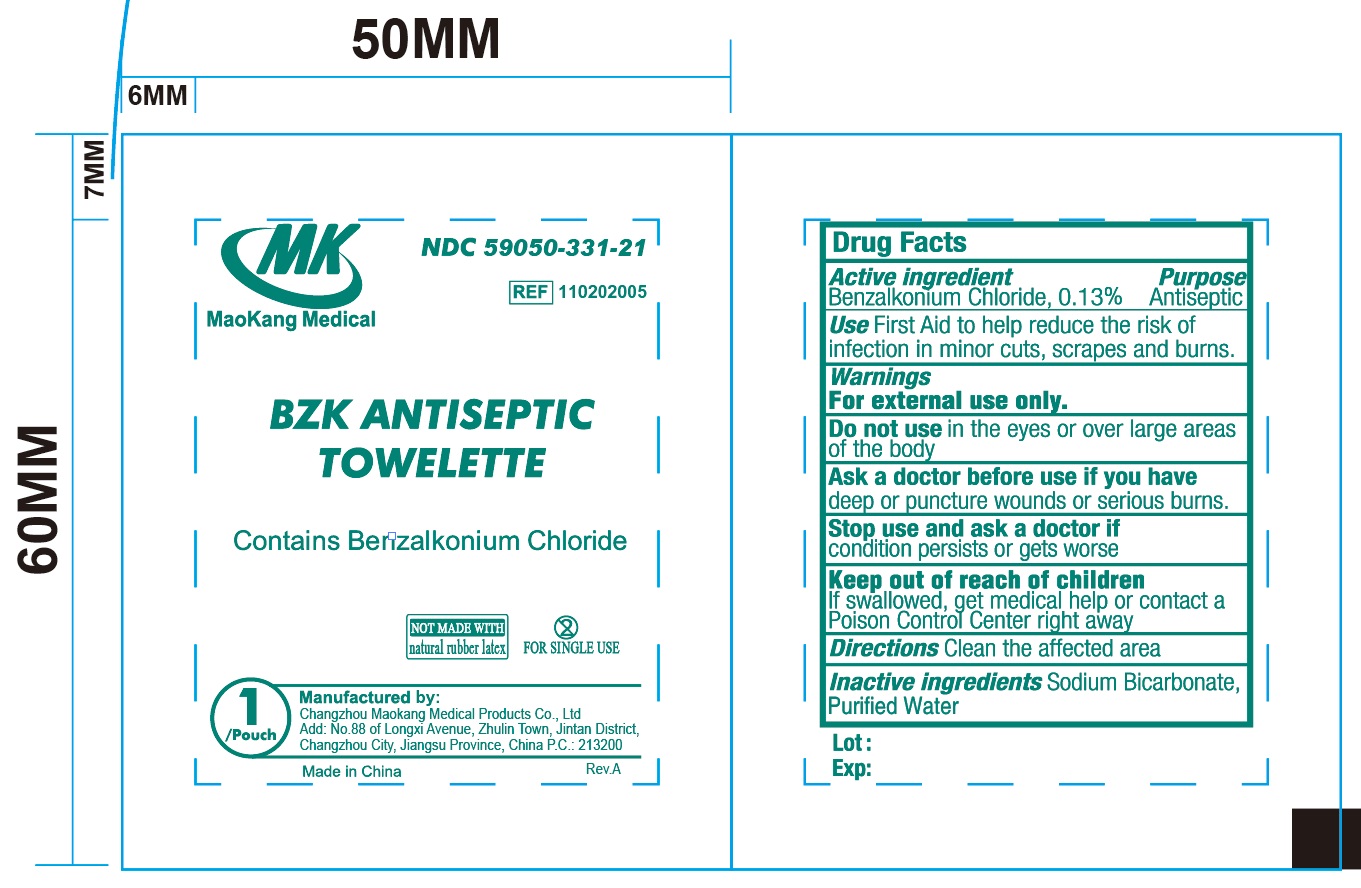 DRUG LABEL: Handy Solutions First Aid Kit
NDC: 67751-228 | Form: KIT | Route: TOPICAL
Manufacturer: Navajo Manufacturing Company Inc.
Category: otc | Type: HUMAN OTC DRUG LABEL
Date: 20240416

ACTIVE INGREDIENTS: BENZALKONIUM CHLORIDE 1.3 mg/1 mL
INACTIVE INGREDIENTS: WATER; SODIUM BICARBONATE

Handy Solutions First Aid Kit

Active ingredient

Benzalkonium Chloride, 0.13%

Purpose

Antiseptic

Use

First Aid to help reduce the risk of infection in minor cuts, scrapes and burns.

Warnings

For external use only.

Do not use in the eyes or over large areas of the body

Ask a doctor before use if you have deep or puncture wounds or serious burns.

Stop use and ask a doctor if condition persists or gets worse

Keep out of reach of children. If swallowed, get medical help or contact a Poison Control center right away

Directions

Antiseptic Wipes:

Clean the affected area.

Bandages:

Anti-bacterial bandages are to be applied topically to the skin for the management of minor cuts, minor scrapes

Inactive ingredients

Sodium Bicarbonate, Purified Water